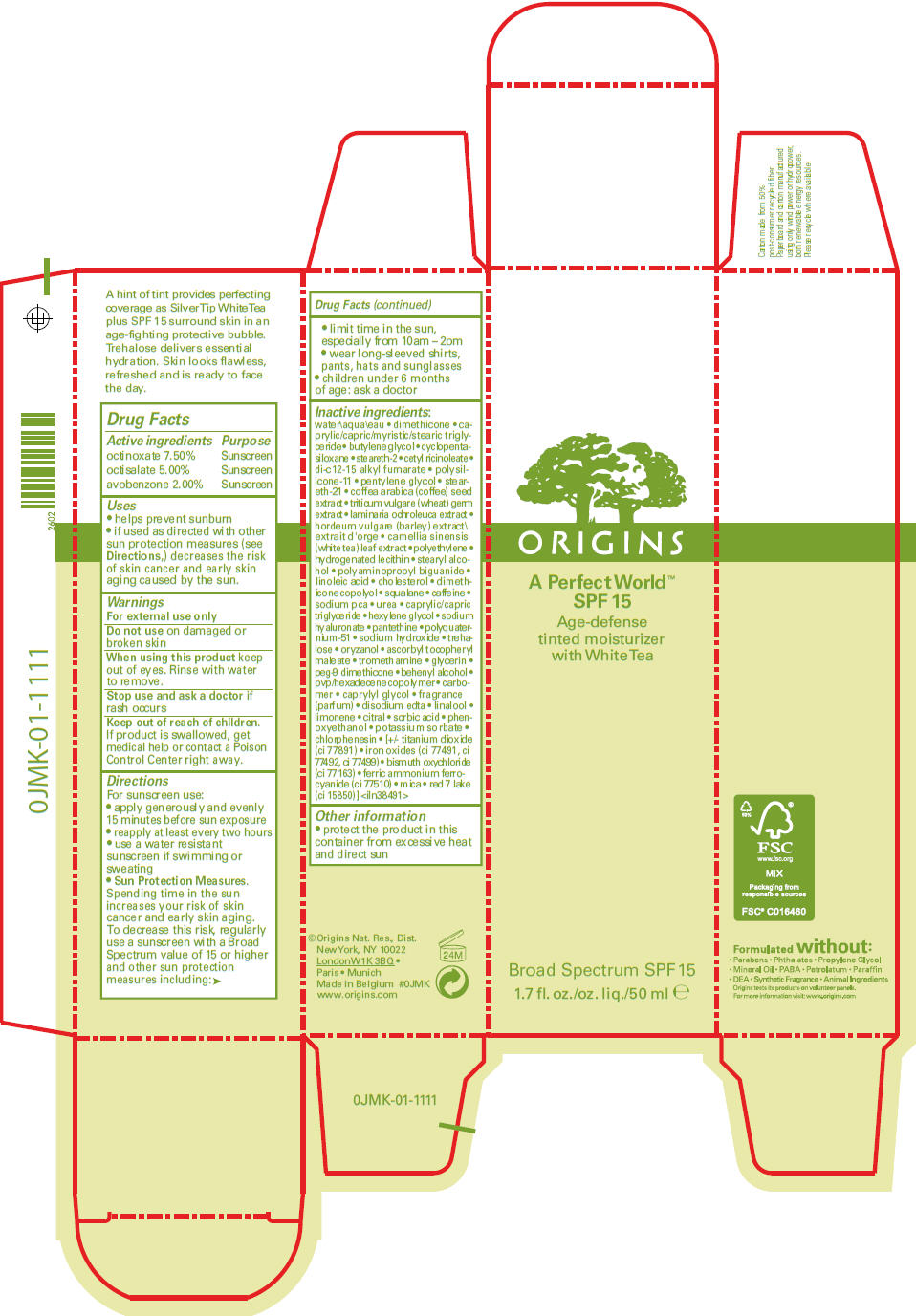 DRUG LABEL: Origins 
NDC: 59427-001 | Form: LIQUID
Manufacturer: ORIGINS NATURAL RESOURCES INC.
Category: otc | Type: HUMAN OTC DRUG LABEL
Date: 20120213

ACTIVE INGREDIENTS: octinoxate 7.5 mL/100 mL; octisalate 5 mL/100 mL; avobenzone 2 mL/100 mL
INACTIVE INGREDIENTS: water; dimethicone; butylene glycol; cyclomethicone 5; steareth-2; cetyl ricinoleate; di-c12-15 alkyl fumarate; pentylene glycol; steareth-21; arabica coffee bean; wheat germ; laminaria ochroleuca; high density polyethylene; stearyl alcohol; polyaminopropyl biguanide; linoleic acid; cholesterol; squalane; caffeine; sodium pyrrolidone carboxylate; urea; medium-chain triglycerides; hexylene glycol; hyaluronate sodium; pantethine; sodium hydroxide; trehalose; gamma oryzanol; tromethamine; glycerin; docosanol; caprylyl glycol; edetate disodium; linalool, (+/-)-; citral; sorbic acid; phenoxyethanol; potassium sorbate; chlorphenesin; titanium dioxide; ferric oxide red; ferric oxide yellow; ferrosoferric oxide; bismuth oxychloride; ferric ammonium ferrocyanide; mica

ORIGINS
A PERFECT WORLD™ AGE DEFENSE TINTED MOISTURIZER SPF 15

Drug Facts

ACTIVE INGREDIENT

Active ingredients | Purpose
octinoxate 7.50% | Sunscreen
octisalate 5.00% | Sunscreen
avobenzone 2.00% | Sunscreen

Uses

- helps prevent sunburn
- if used as directed with other sun protection measures (see Directions,) decreases the risk of skin cancer and early skin aging caused by the sun.

Warnings

For external use only

Do not use on damaged or broken skin

When using this product keep out of eyes. Rinse with water to remove.

STOP USE

Stop use and ask a doctor if rash occurs

Keep out of reach of children. If product is swallowed, get medical help or contact a Poison Control Center right away.

Directions

For sunscreen use:

- apply generously and evenly 15 minutes before sun exposure
- reapply at least every two hours
- use a water resistant sunscreen if swimming or sweating
- Sun Protection Measures.
  Spending time in the sun increases your risk of skin cancer and early skin aging. To decrease this risk, regularly use a sunscreen with a Broad Spectrum value of 15 or higher and other sun protection measures including:
  - limit time in the sun, especially from 10am – 2pm
  - wear long-sleeved shirts, pants, hats and sunglasses
- children under 6 months of age: ask a doctor

Inactive ingredients

water • dimethicone • caprylic/capric/myristic/stearic triglyceride • butylene glycol • cyclopentasiloxane • steareth-2 • cetyl ricinoleate • di-c12-15 alkyl fumarate • polysilicone-11 • pentylene glycol • steareth-21 • coffea arabica (coffee) seed extract • triticum vulgare (wheat) germ extract • laminaria ochroleuca extract • hordeum vulgare (barley) extract\extrait d'orge • camellia sinensis (white tea) leaf extract • polyethylene • hydrogenated lecithin • stearyl alcohol • polyaminopropyl biguanide • linoleic acid • cholesterol • dimethicone copolyol • squalane • caffeine • sodium pca • urea • caprylic/capric triglyceride • hexylene glycol • sodium hyaluronate • pantethine • polyquaternium-51 • sodium hydroxide • trehalose • oryzanol • ascorbyl tocopheryl maleate • tromethamine • glycerin • peg-9 dimethicone • behenyl alcohol • pvp/hexadecene copolymer • carbomer • caprylyl glycol • fragrance • disodium edta • linalool • limonene • citral • sorbic acid • phenoxyethanol • potassium sorbate • chlorphenesin • [+/- titanium dioxide (ci 77891) • iron oxides (ci 77491, ci 77492, ci 77499) • bismuth oxychloride (ci 77163) • ferric ammonium ferrocyanide (ci 77510) • mica • red 7 lake (ci 15850)] <iln38491>

Other information

- protect the product in this container from excessive heat and direct sun

©Origins Nat. Res., Dist. New York, NY 10022

PRINCIPAL DISPLAY PANEL - 50 ml Bottle Carton

ORIGINS

A Perfect World™
SPF 15

Age-defense
tinted moisturizer
with White Tea

Broad Spectrum SPF 15

1.7 fl. oz./50 ml e